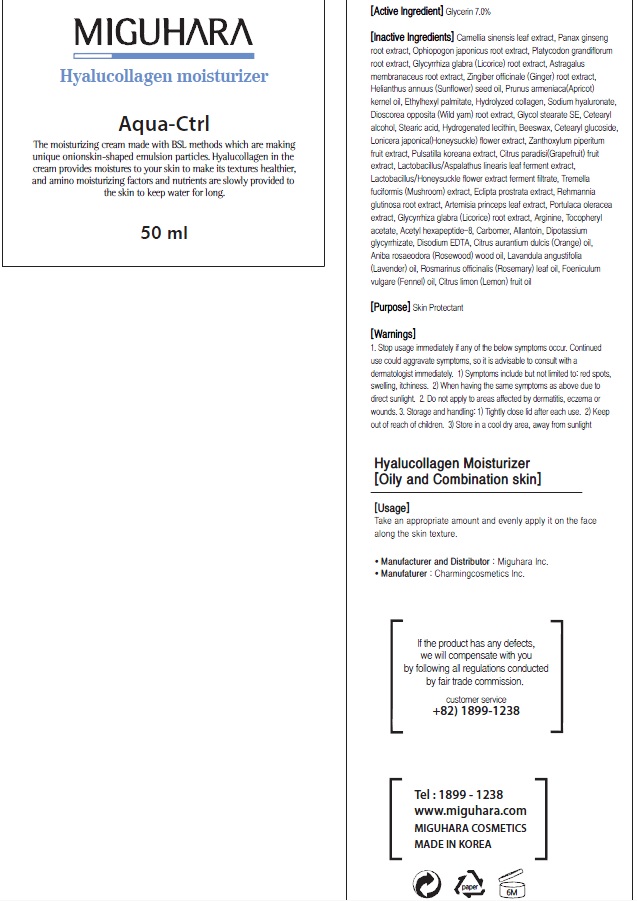 DRUG LABEL: Hyalucollagen Moisturizer
NDC: 70380-250 | Form: CREAM
Manufacturer: MIGUHARA
Category: otc | Type: HUMAN OTC DRUG LABEL
Date: 20160222

ACTIVE INGREDIENTS: Glycerin 3.5 g/50 mL
INACTIVE INGREDIENTS: GREEN TEA LEAF; PANAX GINSENG ROOT WATER

ACTIVE INGREDIENT

Active Ingredient: Glycerin 7.0%

INACTIVE INGREDIENT

Inactive Ingredients: Camellia sinensis leaf extract, Panax ginseng root extract, Ophiopogon japonicus root extract, Platycodon grandiflorum root extract, Glycyrrhiza glabra (Licorice) root extract, Astragalus membranaceus root extract, Zingiber officinale (Ginger) root extract, Helianthus annuus (Sunflower) seed oil, Prunus armeniaca(Apricot) kernel oil, Ethylhexyl palmitate, Hydrolyzed collagen, Sodium hyaluronate, Dioscorea opposita (Wild yam) root extract, Glycol stearate SE, Cetearyl alcohol, Stearic acid, Hydrogenated lecithin, Beeswax, Cetearyl glucoside, Lonicera japonica(Honeysuckle) flower extract, Zanthoxylum piperitum fruit extract, Pulsatilla koreana extract, Citrus paradisi(Grapefruit) fruit extract, Lactobacillus/Aspalathus linearis leaf ferment extract, Lactobacillus/Honeysuckle flower extract ferment filtrate, Tremella fuciformis (Mushroom) extract, Eclipta prostrata extract, Rehmannia glutinosa root extract, Artemisia princeps leaf extract, Portulaca oleracea extract, Glycyrrhiza glabra (Licorice) root extract, Arginine, Tocopheryl acetate, Acetyl hexapeptide-8, Carbomer, Allantoin, Dipotassium glycyrrhizate, Disodium EDTA, Citrus aurantium dulcis (Orange) oil, Aniba rosaeodora (Rosewood) wood oil, Lavandula angustifolia (Lavender) oil, Rosmarinus officinalis (Rosemary) leaf oil, Foeniculum vulgare (Fennel) oil, Citrus limon (Lemon) fruit oil

PURPOSE

Purpose: Skin Protectant

WARNINGS

1. Stop usage immediately if any of the below symptoms occur. Continued use could aggravate symptoms, so it is advisable to consult with a dermatologist immediately. 1) Symptoms include but not limited to: red spots, swelling, itchiness. 2) When having the same symptoms as above due to direct sunlight. 2. Do not apply to areas affected by dermatitis, eczema or wounds. 3. Storage and handling: 1) Tightly close lid after each use. 2 Keep out of reach of children 3) Store in a cool dry area, away from sunlight

KEEP OUT OF REACH OF CHILDREN

Usage

Usage: Apply smoothly on the entire face in the morning and night.

Usage

Usage: Apply smoothly on the entire face in the morning and night.